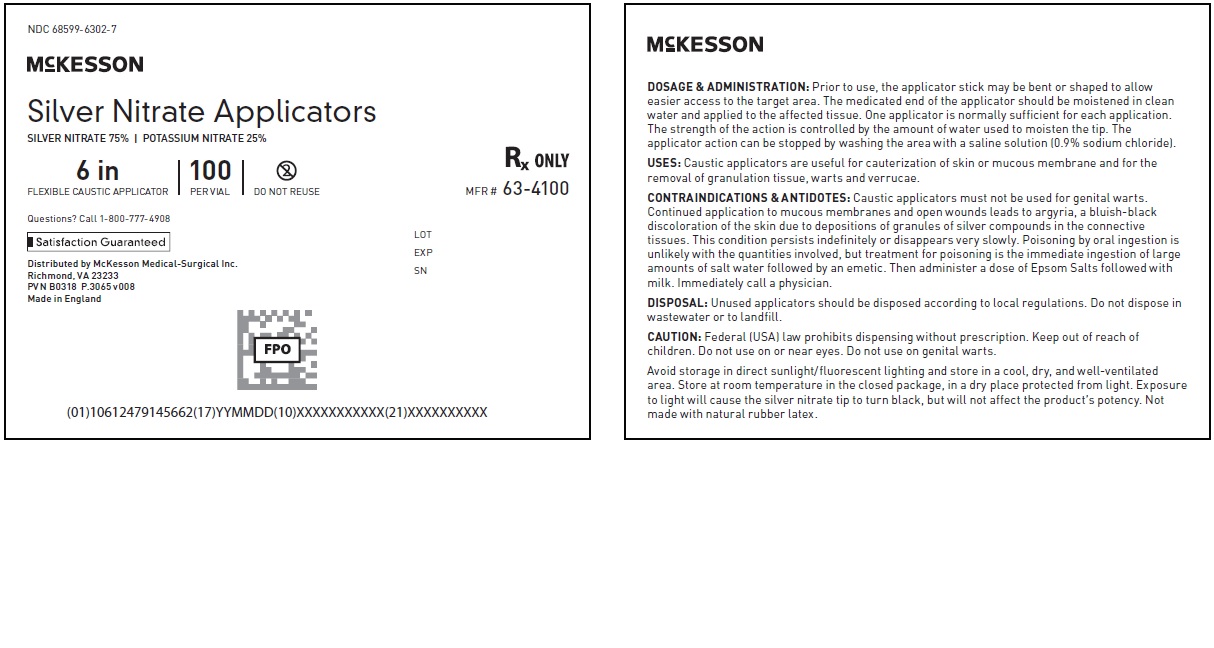 DRUG LABEL: SILVER NITRATE  POTASSIUM NITRATE
NDC: 68599-6302 | Form: STICK
Manufacturer: McKesson Medical-Surgical
Category: prescription | Type: HUMAN PRESCRIPTION DRUG LABEL
Date: 20210115

ACTIVE INGREDIENTS: POTASSIUM NITRATE 75 mg/1 g; SILVER NITRATE 25 mg/1 g

Silver Nitrate Applicators

McKESSON
Silver Nitrate Applicators
Silver NITRATE 75%
POTASSIUM NITRATE 25%

Rx Only

DOSAGE & ADMINISTRATION:
Prior to use, the applicator stick may be bent or shaped to allow easier access to the target area. The
medicated end of the applicator should be moistened in clean water and applied to the affected tissue.
One applicator is normally sufficient for each application. The strength of the action is controlled by
the amount of water used to moisten the tip. The applicator action can be stopped by washing the area
with a saline solution (0.9% sodium chloride).

USES:
Caustic applicators are useful for cauterization of skin or mucous membrane and for the removal of
granulation tissue, warts and verrucae.

CONTRAINDICATIONS & ANTIDOTES:
Caustic applicators must not be used for genital warts. Continued application to mucous membranes and
open wounds leads to argyria, a bluish-black discoloration of the skin due to depositions of granules of
silver compounds in the connective tissues.
This condition persists indefinitely or disappears very slowly. Poisoning by oral ingestion is unlikely
with the quantities involved, but treatment for poisoning is the immediate ingestion of large amounts of
salt water followed by an emetic. Then administer a dose of Epsom Salts followed with milk.
Immediately call a physician.

WARNINGS AND PRECAUTIONS

CAUTION:
Federal (USA) law prohibits dispensing without prescription.

Keep out of reach of children.
Do not use on or near eyes. Do not use on genital warts.
Avoid storage in direct sunlight/fluorescent lighting and store in a cool, dry, and well-ventilated area.
Store at room temperature in the closed package, in a dry place protected from light. Exposure to light
will cause the silver nitrate tip to turn black, but will not affect the product's potency.
Not made with natural rubber latex.

Questions? Call 1-800-777-4908
Distributed by McKesson Medical-Surgical Inc.
Richmond, VA 23233
PVN A0417
Made in England

PACKAGE LABEL

NDC 68599-6302-7

McKesson
Silver Nitrate Applicators MFR # 63-4100
SILVER NITRATE 75% | POTASSIUM NITRATE 25%
6 in
FLEXIBLE CAUSTIC APPLICATOR
100
PER VIAL
DO NOT REUSE
Questions? Call 1-800-777-4908
Distributed by McKesson Medical-Surgical Inc.
Richmond, VA 23233
PVN B0118 P.3065 v008
Made in England